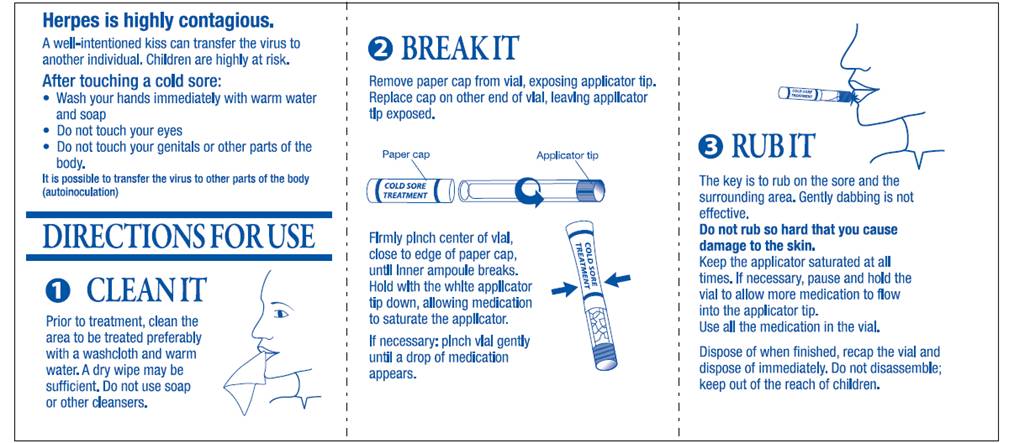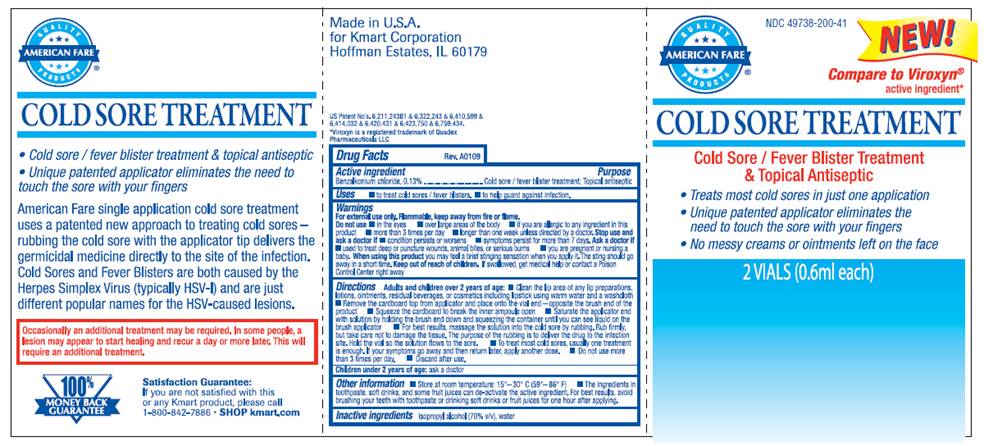 DRUG LABEL: Cold Sore Treatment
NDC: 49738-200 | Form: TINCTURE
Manufacturer: Kmart Corporation
Category: otc | Type: HUMAN OTC DRUG LABEL
Date: 20100415

ACTIVE INGREDIENTS: Benzalkonium chloride 0.13 mL/1 mL
INACTIVE INGREDIENTS: isopropyl alcohol; water

DRUG FACTS

ACTIVE INGREDIENT

Benzalkonium chloride, 0.13%

PURPOSE

Cold Sore / Fever Blister Treatment; Topical Antiseptic

USES

- Treat cold sores / fever blisters
- Help guard against infection

WARNINGS

For external use only. Flammable, keep away from fire or flame.

Do not use

- in the eyes
- over large areas of the body
- if you are allergic to any ingredient in the product
- more than 3 times per day
- longer than one week unless directed by a doctor.

Stop use and ask a doctor if

- condition persists or worsens
- symptoms persist for more than 7 days

Ask a doctor if

- used to treat deep or puncture wounds, animal bites, or serious burns
- you are pregnant or nursing a baby

When using this product

you may feel a brief stinging sensation when applying it. The sting should go away in a short time.

Keep out of reach of children

If swallowed, get medical help or contact a Poison Control Center right away.

DIRECTIONS

Adults and children over 2 years of age:

- Clean the lip area of any lip preparations, lotions, ointments, residual beverages, or cosmetics including lipstick using warm water and a washcloth
- Remove the cardboard top from applicator and place onto the glass/plastic vial end - opposite the brush end of the product
- Squeeze the cardboard to break the inner glass vial open
- Saturate the applicator end with solution by holding the brush end down and squeezing the container until you can see liquid on the brush applicator
- For best results, massage the solution into the cold sore by rubbing. Rub firmly, but take care not to damage the tissue. The purpose of the rubbing is to deliver the drug to the infection site. Hold the vial so the solution flows to the sore.
- To treat most cold sores, usually one treatment is enough.
- If your symptoms go away and then return later, apply another dose.
- Do not use more than 3 times per day
- Discard after use.

Children under 2 years of age: ask a doctor.

OTHER INFORMATION

- Store at room temperature: 15° - 30° C (59° - 86° F)
- The ingredients in toothpaste, softdrinks, and some fruit juices can de-activate the active ingredient. For best results, avoid brushing your teeth with toothpaste or drinking soft drinks or fruit juices for one hour after applying.

INACTIVE INGREDIENTS

isopropyl alcohol, water

PACKAGE INFORMATION - TRIFOLD INNER

Herpes is highly contagious.
A well-intentioned kiss can transfer the virus to another individual. Children are highly at risk.
After touching a cold sore:

- Wash your hands immediately with warm water and soap
- Do not touch your eyes
- Do not touch your genitals or other parts of the body

It is possible to transfer the virus to other parts of the body (autoinoculation)
1. CLEAN IT
Prior to treatment, clean the area to be treated preferably with a washcloth and warm water. A dry wipe may be sufficient. Do not use soap or other cleansers.
2. BREAK IT
Remove paper cap from vial, exposing applicator tip.
Replace cap on other end of vial, leaving applicator tip exposed.
Firmly pinch center of vial, close to edge of paper cap, until inner ampoule breaks.
Hold with the white applicator tip down, allowing medication to saturate the applicator.
If necessary: pinch vial gently until a drop of medication appears.
Prior to use: Remove vial from package
3. RUB IT
The key is to rub on the sore and the surrounding area. Gently dabbing is not effective.
Do not rub so hard that you cause damage to the skin.
Keep the applicator saturated at all times. If necessary, pause and hold the vial to allow more medication to flow into the applicator tip.
Use all the medication in the vial.
Dispose of when finished, recap the vial and dispose of immediately. Do not disassemble; keep out of reach of children.

PACKAGE INFORMATION - TRIFOLD OUTER

NDC 49738-200-41
AMERICAN FARE®
NEW!
Compare to Viroxyn® active ingredient*
COLD SORE TREATMENT
Cold Sore / Fever Blister Treatment
and Topical Antiseptic

- Treats most cold sores in just one application
- Unique patented applicator eliminates the need to touch the sore with your fingers
- No messy creams or ointments left on the face

2 VIALS (0.6 ml each)
Made in U.S.A.
for Kmart Corporation
Hoffman Estates, IL 60179
US Patent No’s 6,211,243B1 and 6,322,243 and 6,410,599 and
6,414,032 and 6,420,431 and 6,423,750 and 6,759,434.
*Viroxyn® is a registered trademark of Quadex Pharmaceuticals, LLC
COLD SORE TREATMENT

- Cold Sore / Fever Blister Treatment and Topical Antiseptic
- Unique patented applicator eliminates the need to touch the sore with your fingers

American Fare single application cold sore treatment uses a patented new approach to treating cold sores - rubbing the cold sore
with the applicator tip delivers the germicidal medicine directly to
the site of the infection. Cold Sores and Fever Blisters are both caused by the Herpes Simplex virus (typically HSV-1) and are just different popular names for the HSV-caused lesions.
Occasionally an additional treatment may be required. In some people, a lesion may appear to start healing and recur a day or more later. This will require an additional treatment.
Satisfaction Guarantee:
If you are not satisfied with this or any Kmart Product, please call 1-800-842-7826. SHOP kmart.com